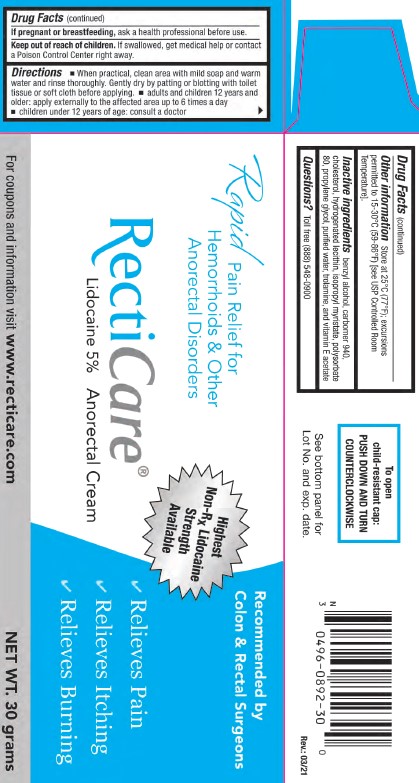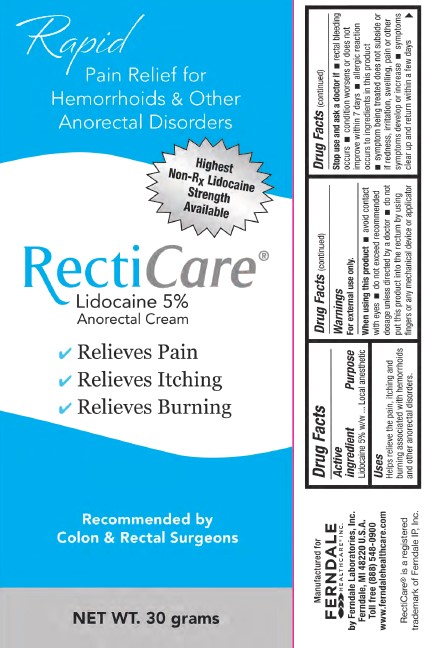 DRUG LABEL: RECTICARE
NDC: 0496-0892 | Form: CREAM
Manufacturer: Ferndale Laboratories, Inc.
Category: otc | Type: HUMAN OTC DRUG LABEL
Date: 20241217

ACTIVE INGREDIENTS: LIDOCAINE 50 mg/1 g
INACTIVE INGREDIENTS: CHOLESTEROL; LECITHIN, SOYBEAN; ISOPROPYL MYRISTATE; POLYSORBATE 80; PROPYLENE GLYCOL; WATER; TROLAMINE; ALPHA-TOCOPHEROL ACETATE; BENZYL ALCOHOL; CARBOMER HOMOPOLYMER TYPE C

RECTICARE Lidocaine 5% Anorectal Cream

Active ingredient

Lidocaine 5% w/w

Purpose

Local anesthetic

Uses

Helps relieve the pain, itching, and burning associated with hemorrhoids and other anorectal disorders.

Warnings

For external use only.

When using this product

- avoid contact with eyes
- do not exceed recommended dosage unless directed by a doctor
- do not put this product into the rectum by using fingers or any mechanical device or applicator

Stop use and ask a doctor if

- rectal bleeding occurs
- condition worsens or does not improve within 7 days
- allergic reaction occurs to ingredients in this product
- symptom being treated does not subside or if redness, irritation, swelling, pain or other symptoms develop or increase
- symptoms clear up and return within a few days

If pregnant or breastfeeding,

ask a health professional before use.

Keep out of reach of children.

If swallowed, get medical help or contact a Poison Control Center right away.

Directions

- When practical, clean area with mild soap and warm water and rinse thoroughly. Gently dry by patting or blotting with toilet tissue or soft cloth before applying.
- Adults and children 12 years and older: apply externally to the affected area up to 6 times a day.
- Children under 12 years of age: consult a doctor.
- To use finger cots: Roll one finger cot over finger. Gently squeeze cream onto finger cot. Smooth a layer of the cream over affected area.

Other Information

Store at 25°C (77°F); excursions permitted to 15-30°C (59-86°F) [see USP Controlled Room Temperature].

Inactive Ingredients

benzyl alcohol, carbomer 940, cholesterol, hydrogenated lecithin, isopropyl myristate, polysorbate 80, propylene glycol, purified water, trolamine, and vitamin E acetate